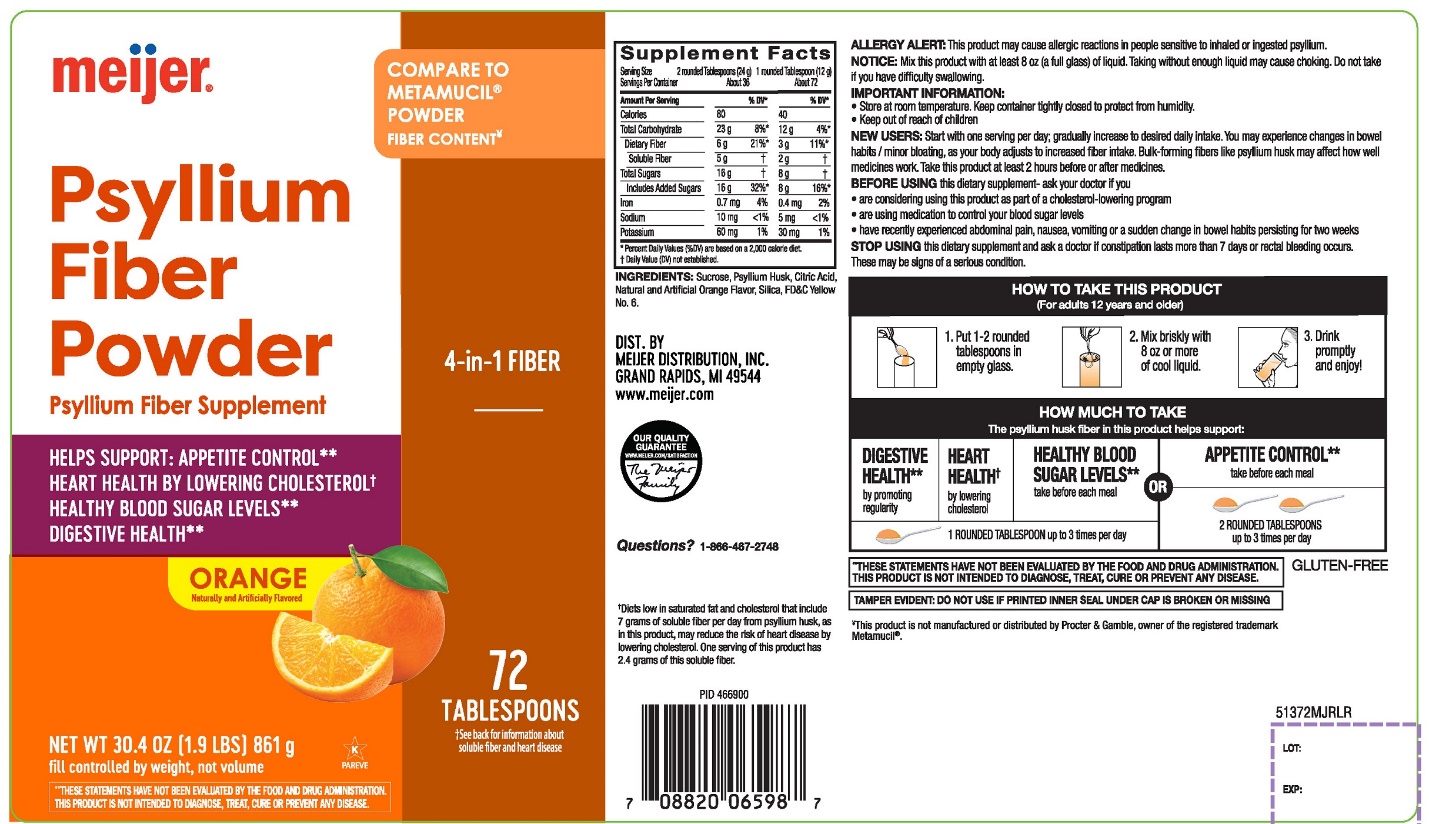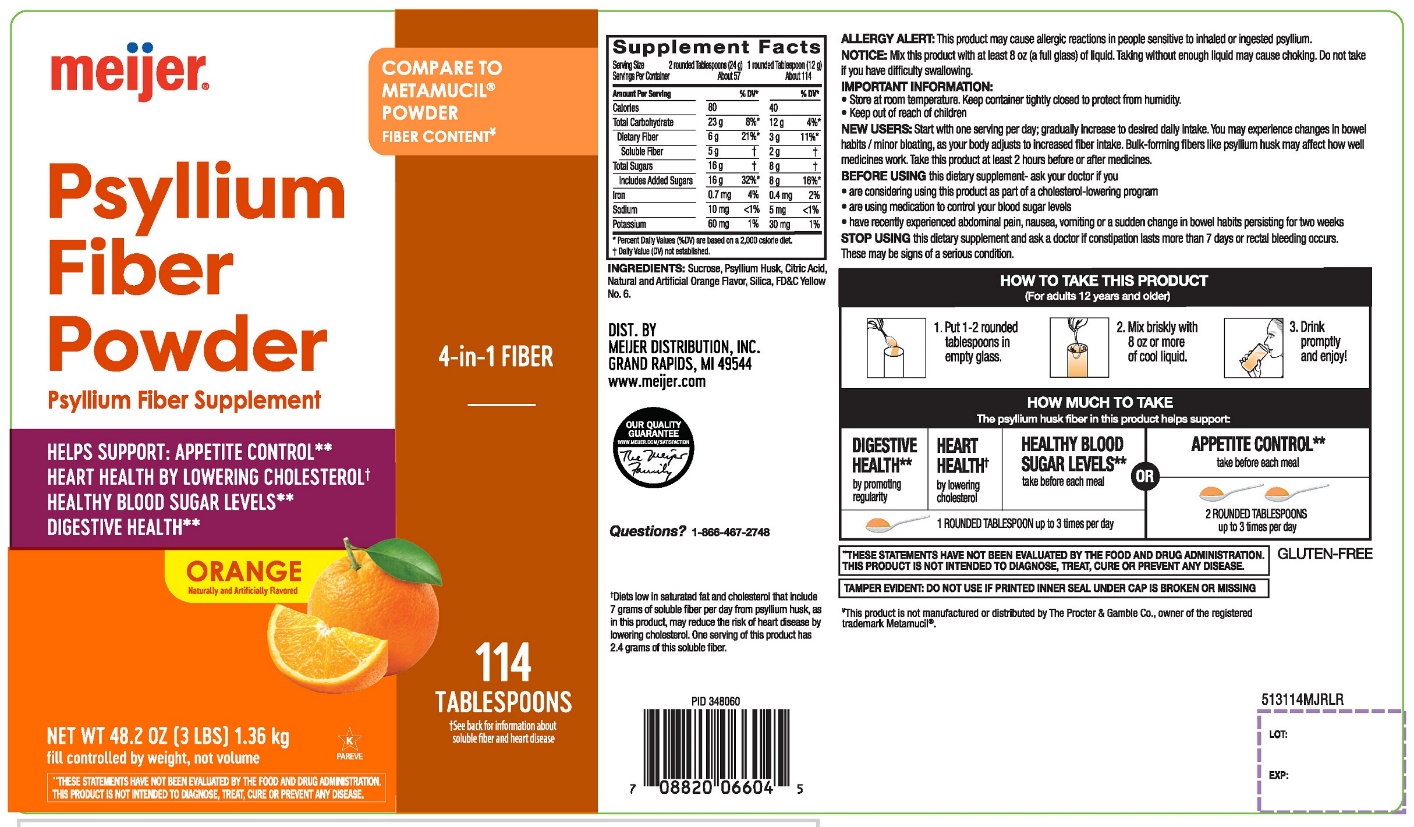 DRUG LABEL: meijer Natural Fiber
NDC: 41250-914 | Form: POWDER
Manufacturer: MEIJER DISTRIBUTION INC
Category: otc | Type: HUMAN OTC DRUG LABEL
Date: 20251024

ACTIVE INGREDIENTS: PSYLLIUM HUSK 3.4 g/12 g
INACTIVE INGREDIENTS: ANHYDROUS CITRIC ACID; FD&C YELLOW NO. 6; SILICON DIOXIDE; SUCROSE

meijer®Natural Fiber 100% Natural Psyllium Husk Orange Flavor 114 TABLESPOONS

Drug Facts

Active ingredient: (in each TABLESPOON)

Psyllium husk approximately 3.4 g

Purpose

Bulk-forming Laxative

Uses:

- for relief of occasional constipation (irregularity)
- Generally produces bowel movement in 12-72 hours

Warnings:

Choking

Taking this product without adequate fluid may cause it to swell and block your throat or esophagus and may cause choking. Do not take this product if you have difficulty in swallowing. If you experience chest pain, vomiting, or difficulty in swallowing or breathing after taking this product, seek immediate medical attention.

Allergy alert:

This product may cause allergic reaction in people sensitive to inhaled or ingested psyllium.

Ask a doctor before use if you have

- a sudden change in bowel habits persisting for 2 weeks
- abdominal pain, nausea or vomiting

Stop use and ask a doctor if

- constipation lasts more than 7 days
- rectal bleeding occurs

These may be signs of a serious condition.

Keep out of reach of children.In case of overdose, get medical help or contact a Poison Control Center right away at 1-800-222-1222.

Directions:

Put one dose into an empty glass. Mix this product (child or adult dose) with at least 8 ounces (a full glass) of water or other fluid. Taking this product without enough liquid may cause choking. See choking warning. Stir briskly and drink promptly. If mixture thickens, add more liquid and stir.

Adults & children 12 years & older: | 1 rounded TABLESPOON in 8 ounces of liquid at the first sign of irregularity. Can be taken up to 3 times daily.
Children 6 – 11 yrs : | ½ adult dose in 8 ounces of liquid, up to 3 times daily
Children Under 6 yrs: | Consult a doctor

Bulk forming fibers like psyllium husk may affect how well other medicines work. If you are taking a prescription medicine by mouth, take this product at least 2 hours before or 2 hours after the prescribed medicine.

New Users

Start with 1 serving per day; gradually increased to desired daily intake. You may initially experience changes in bowel habits or minor bloating, as your body adjusts to increased fiber intake.

Other information:

- each tablespoon contains:potassium 35 mg; sodium 5 mg
- store at room temperature. tightly closed to protect from humidity
- contains a 100% natural, therapeutic fiber

Inactive ingredients

citric acid, FD & C yellow 6, natural and artificial orange flavor, silica, sucrose

Questions or comments?

1-866-467-2748

PRINCIPAL DISPLAY PANEL

meijer®

Compare to the active ingredient in Metamucil®4 in 1 MultiHealth Fiber*

Gluten Free

Natural Fiber

100%NATURAL PSYLLIUM HUSK

Multi- Benefit Daily Fiber Supplement

Therapy for Regularity

- Helps you feel less hungrybetween meals**
- Helps maintain healthy blood sugarlevels as part of your diet **
- Helps lower cholesterolto promote heart health**
- Promotes digestive health**

ORANGE SMOOTH

NATURALLY & ARTIFICIALLY FLAVORED

114 TABLESPOON‡

NET WT 48.2 OZ (3 LB) 1366 g

FILL CONTROLLED BY WEIGHT, NOT VOLUME

†See back for information about soluble fiber and heart disease.

‡Serving size varies. See DIRECTIONS on back panel for more information

**These statements have not been evaluated by the Food and Drug Administration. This product is not intended to diagnose, treat, cure or prevent any disease.

DO NOT USE IF PRINTED INNER SEAL IS BROKEN OR MISSING

*This product is not manufactured or distributed by Procter & Gamble Company, Owner of the registered trademark Metamucil ®.

SF SUGAR FREE

GF GLUTEN FREE

GLUTEN FREE.

If you have specific dietary needs, you should consult your doctor before consuming this product.

This product has a low glycemic index, a measure of the effect of dietary carbohydrates on blood sugar levels.

MEIJER PHARAMACISTS RECOMMEND

MONEY BACK GUARANTEE

DIST. BY MEIJER DISTRIBUTION, INC.

GRAND RAPIDS, MI 49544

www.meijer.com